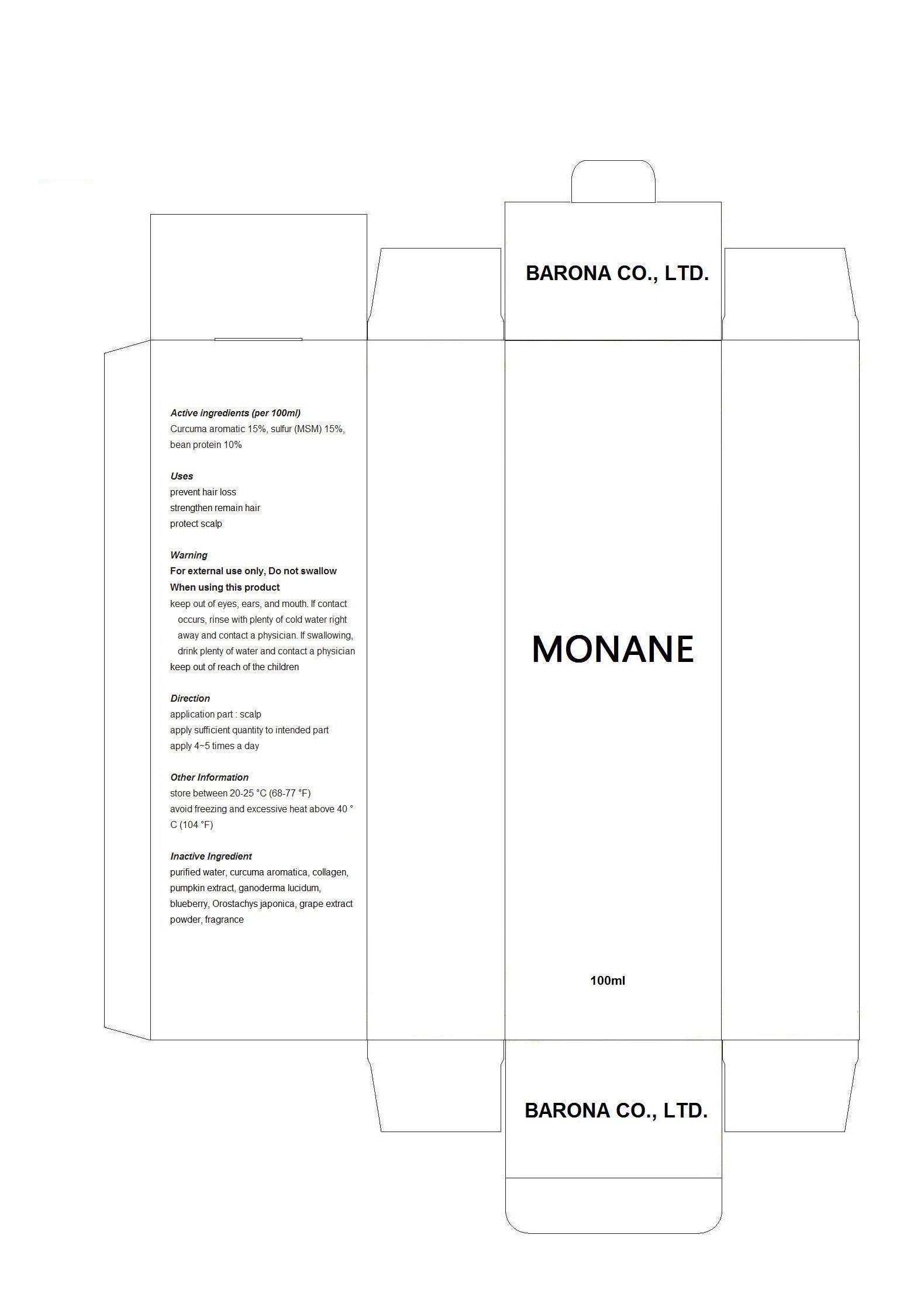 DRUG LABEL: Luxuriant hair for solutions
NDC: 61164-7001 | Form: LIQUID
Manufacturer: Barona Co., Ltd 
Category: otc | Type: HUMAN OTC DRUG LABEL
Date: 20160203

ACTIVE INGREDIENTS: PEPPERMINT OIL 0.1 g/100 g
INACTIVE INGREDIENTS: WATER; CHELIDONIUM MAJUS

Drug Facts

ACTIVE INGREDIENT

CURCUMA AROMATICA ROOT OIL

INACTIVE INGREDIENT

sulfur (MSM), bean protein, purified water, curcuma aromatica, collagen, pumpkin extract, ganoderma lucidum, blueberry, Orostachys japonica, grape extract powder, fragrance

PURPOSE

prevent hair loss
strengthen remain hair
protect scalp

keep out or reach of the children

INDICATIONS AND USAGE

apply 4% times everyday to the scalp and rub softly

WARNINGS

do not swallow

DOSAGE AND ADMINISTRATION

for topical use only